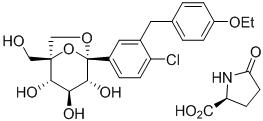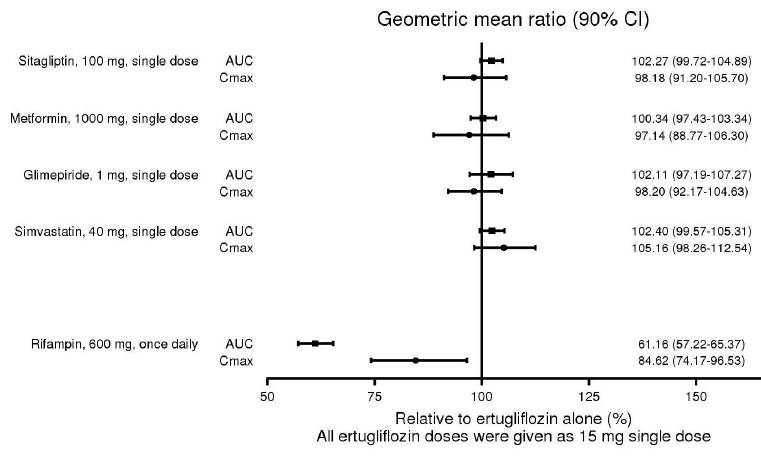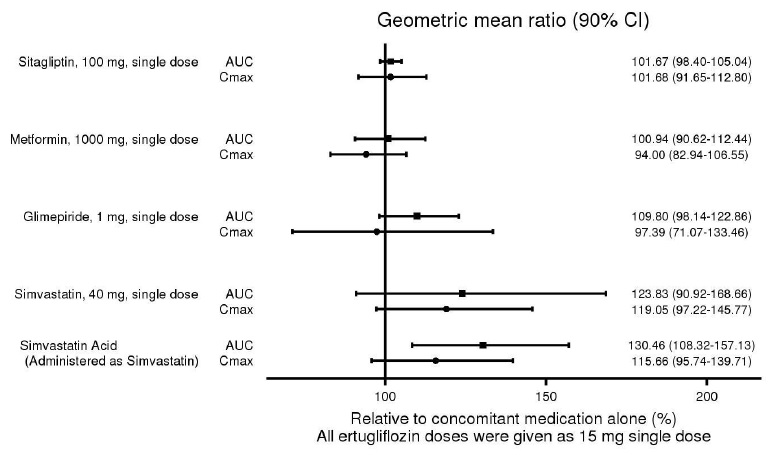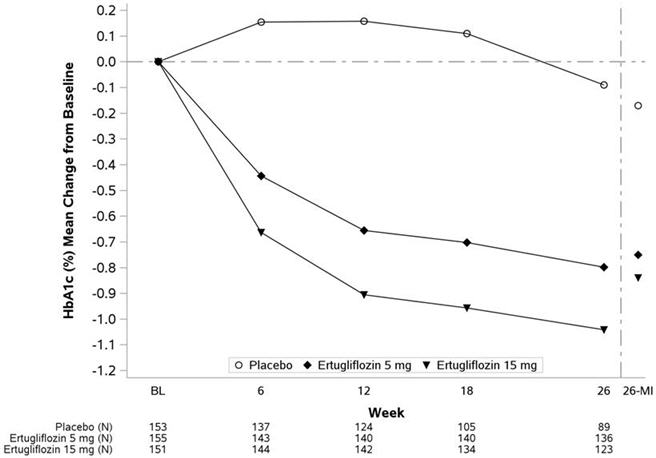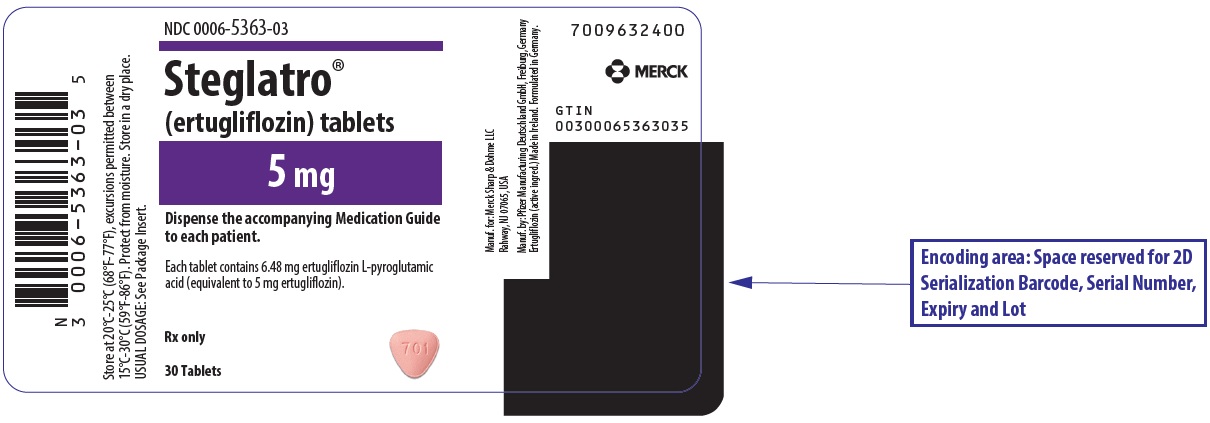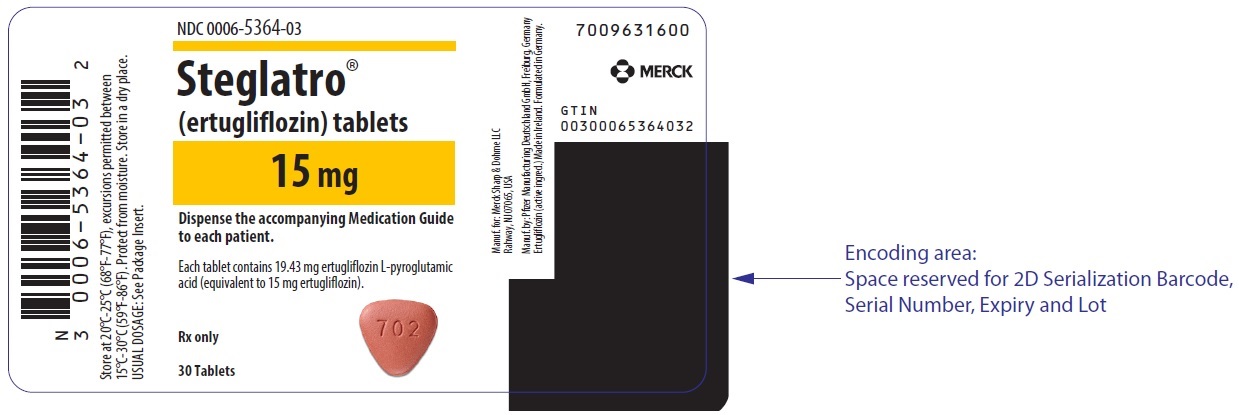 DRUG LABEL: STEGLATRO
NDC: 0006-5363 | Form: TABLET, FILM COATED
Manufacturer: Merck Sharp & Dohme LLC
Category: prescription | Type: HUMAN PRESCRIPTION DRUG LABEL
Date: 20241220

ACTIVE INGREDIENTS: ERTUGLIFLOZIN PIDOLATE 5 mg/1 1
INACTIVE INGREDIENTS: MICROCRYSTALLINE CELLULOSE; LACTOSE MONOHYDRATE; SODIUM STARCH GLYCOLATE TYPE A POTATO; MAGNESIUM STEARATE; HYPROMELLOSE 2910 (6 MPA.S); POLYETHYLENE GLYCOL 3350; TRIACETIN; TITANIUM DIOXIDE; FERRIC OXIDE RED

HIGHLIGHTS OF PRESCRIBING INFORMATION

These highlights do not include all the information needed to use STEGLATRO safely and effectively. See full prescribing information for STEGLATRO.
STEGLATRO® (ertugliflozin) tablets, for oral use
Initial U.S. Approval: 2017

RECENT MAJOR CHANGES

Dosage and Administration (2.3) | 12/2024
Warnings and Precautions (5.2, 5.5) | 12/2024

1 INDICATIONS AND USAGE

STEGLATRO is a sodium glucose co-transporter 2 (SGLT2) inhibitor indicated as an adjunct to diet and exercise to improve glycemic control in adults with type 2 diabetes mellitus. (1)

Limitations of Use:

Not recommended for use to improve glycemic control in patients with type 1 diabetes mellitus. (1)

2 DOSAGE AND ADMINISTRATION

- Assess renal function before initiating and as clinically indicated. (2.1)
- Correct volume depletion before initiating STEGLATRO. (2.1)
- Recommended starting dosage is 5 mg orally once daily, taken in the morning, with or without food. (2.2)
- Increase dosage to 15 mg orally once daily in those tolerating STEGLATRO and needing additional glycemic control. (2.2)
- Use is not recommended in patients with an estimated glomerular filtration rate (eGFR) less than 45 mL/min/1.73 m^2. (2.2)
- Withhold STEGLATRO for at least 4 days, if possible, prior to surgery or procedures associated with prolonged fasting. (2.3)

3 DOSAGE FORMS AND STRENGTHS

Tablets: 5 mg and 15 mg

4 CONTRAINDICATIONS

- Hypersensitivity to ertugliflozin or any of the excipients in STEGLATRO. (4)

5 WARNINGS AND PRECAUTIONS

- Diabetic Ketoacidosis in Patients with Type 1 Diabetes Mellitus and Other Ketoacidosis: Consider ketone monitoring in patients at risk for ketoacidosis, as indicated. Assess for ketoacidosis regardless of presenting blood glucose levels and discontinue STEGLATRO if ketoacidosis is suspected. Monitor patients for resolution of ketoacidosis before restarting. (5.1)
- Lower Limb Amputation: Monitor patients for infections or ulcers of lower limbs, and discontinue if these occur. (5.2)
- Volume Depletion: May result in acute kidney injury. Before initiating, assess and correct volume status in patients with renal impairment or low systolic blood pressure, elderly patients, or patients on diuretics. Monitor for signs and symptoms during therapy. (5.3)
- Urosepsis and Pyelonephritis: Evaluate patients for signs and symptoms of urinary tract infections and treat promptly, if indicated. (5.4)
- Hypoglycemia: Consider a lower dose of insulin or insulin secretagogue to reduce risk of hypoglycemia when used in combination. (5.5)
- Necrotizing Fasciitis of the Perineum (Fournier's Gangrene): Serious, life-threatening cases have occurred in both females and males. Assess patients presenting with pain or tenderness, erythema, or swelling in the genital or perineal area, along with fever or malaise. If suspected, institute prompt treatment. (5.6)
- Genital Mycotic Infections: Monitor and treat if indicated. (5.7)

6 ADVERSE REACTIONS

Most common adverse reactions (incidence ≥ 5%) were female genital mycotic infections. (6.1)

To report SUSPECTED ADVERSE REACTIONS, contact Merck Sharp & Dohme LLC at 1-877-888-4231 or FDA at 1-800-FDA-1088 or www.fda.gov/medwatch.

7 DRUG INTERACTIONS

See full prescribing information for information on drug interactions and interference of STEGLATRO with laboratory tests. (7)

8 USE IN SPECIFIC POPULATIONS

- Pregnancy: Advise females of the potential risk to a fetus especially during the second and third trimesters. (8.1)
- Lactation: Breastfeeding not recommended. (8.2)
- Geriatrics: Higher incidence of adverse reactions related to reduced intravascular volume. (8.5)
- Renal Impairment: Higher incidence of adverse reactions related to reduced intravascular volume and renal function. (8.6)

FULL PRESCRIBING INFORMATION

1 INDICATIONS AND USAGE

STEGLATRO® is indicated as an adjunct to diet and exercise to improve glycemic control in adults with type 2 diabetes mellitus.

Limitations of Use

- Not recommended for use to improve glycemic control in patients with type 1 diabetes mellitus [see Warnings and Precautions (5.1)].

2 DOSAGE AND ADMINISTRATION

2.1 Prior to Initiation of STEGLATRO

- Assess renal function before initiating STEGLATRO and as clinically indicated [see Warnings and Precautions (5.3)].
- Assess volume status. In patients with volume depletion, correct this condition before initiating STEGLATRO [see Warnings and Precautions (5.3) and Use in Specific Populations (8.5, 8.6)].

2.2 Recommended Dosage

- The recommended starting dosage of STEGLATRO is 5 mg orally once daily, taken in the morning, with or without food.
- For additional glycemic control, the dosage may be increased to 15 mg orally once daily in patients tolerating STEGLATRO.
- Use of STEGLATRO is not recommended in patients with an estimated glomerular filtration rate (eGFR) less than 45 mL/min/1.73 m^2.

2.3 Temporary Interruption for Surgery

Withhold STEGLATRO for at least 4 days, if possible, prior to surgery or procedures associated with prolonged fasting. Resume STEGLATRO when the patient is clinically stable and has resumed oral intake [see Warnings and Precautions (5.1) and Clinical Pharmacology (12.2)].

3 DOSAGE FORMS AND STRENGTHS

- Tablets: 5 mg, pink, triangular-shaped debossed with "701" on one side and plain on the other side.
- Tablets: 15 mg, red, triangular-shaped debossed with "702" on one side and plain on the other side.

4 CONTRAINDICATIONS

STEGLATRO is contraindicated in patients with hypersensitivity to ertugliflozin or any excipient in STEGLATRO. Reactions such as angioedema have occurred [see Adverse Reactions (6.2)].

5 WARNINGS AND PRECAUTIONS

5.1 Diabetic Ketoacidosis in Patients with Type 1 Diabetes Mellitus and Other Ketoacidosis

In patients with type 1 diabetes mellitus, STEGLATRO significantly increases the risk of diabetic ketoacidosis, a life-threatening event, beyond the background rate. In placebo-controlled trials of patients with type 1 diabetes mellitus, the risk of ketoacidosis was markedly increased in patients who received sodium glucose transporter 2 (SGLT2) inhibitors compared to patients who received placebo; this risk may be greater with higher doses. STEGLATRO is not indicated for glycemic control in patients with type 1 diabetes mellitus.

Type 2 diabetes mellitus and pancreatic disorders (e.g., history of pancreatitis or pancreatic surgery) are also risk factors for ketoacidosis. There have been postmarketing reports of fatal events of ketoacidosis in patients with type 2 diabetes mellitus using SGLT2 inhibitors.

Precipitating conditions for diabetic ketoacidosis or other ketoacidosis include under-insulinization due to insulin dose reduction or missed insulin doses, acute febrile illness, reduced caloric intake, ketogenic diet, surgery, volume depletion, and alcohol abuse.

Signs and symptoms are consistent with dehydration and severe metabolic acidosis and include nausea, vomiting, abdominal pain, generalized malaise, and shortness of breath. Blood glucose levels at presentation may be below those typically expected for diabetic ketoacidosis (e.g., less than 250 mg/dL). Ketoacidosis and glucosuria may persist longer than typically expected. Urinary glucose excretion persists for 4 days after discontinuing STEGLATRO [see Clinical Pharmacology (12.2)]; however, there have been postmarketing reports of ketoacidosis and/or glucosuria lasting greater than 6 days and some up to 2 weeks after discontinuation of SGLT2 inhibitors.

Consider ketone monitoring in patients at risk for ketoacidosis if indicated by the clinical situation. Assess for ketoacidosis regardless of presenting blood glucose levels in patients who present with signs and symptoms consistent with severe metabolic acidosis. If ketoacidosis is suspected, discontinue STEGLATRO, promptly evaluate, and treat ketoacidosis, if confirmed. Monitor patients for resolution of ketoacidosis before restarting STEGLATRO.

Withhold STEGLATRO, if possible, in temporary clinical situations that could predispose patients to ketoacidosis. Resume STEGLATRO when the patient is clinically stable and has resumed oral intake [see Dosage and Administration (2.3)].

Educate all patients on the signs and symptoms of ketoacidosis and instruct patients to discontinue STEGLATRO and seek medical attention immediately if signs and symptoms occur.

5.2 Lower Limb Amputation

In a long-term cardiovascular outcomes study [see Clinical Studies (14.2)], in patients with type 2 diabetes mellitus and established cardiovascular disease, the occurrence of non-traumatic lower limb amputations was reported with event rates of 4.7, 5.7, and 6.0 events per 1,000 patient-years in the placebo, STEGLATRO 5 mg, and STEGLATRO 15 mg treatment arms, respectively.

Amputation of the toe and foot were most frequent (81 out of 109 patients with lower limb amputations). Some patients had multiple amputations, some involving both lower limbs.

Lower limb infections, gangrene, and diabetic foot ulcers were the most common precipitating medical events leading to the need for an amputation. Patients with amputations were more likely to be male, have higher A1C (%) at baseline, have a history of peripheral arterial disease, amputation or peripheral revascularization procedure, diabetic foot, and to have been taking diuretics or insulin.

Across seven STEGLATRO clinical trials, non-traumatic lower limb amputations were reported in 1 (0.1%) patient in the comparator group, 3 (0.2%) patients in the STEGLATRO 5 mg group, and 8 (0.5%) patients in the STEGLATRO 15 mg group.

Counsel patients about the importance of routine preventative foot care. Monitor patients receiving STEGLATRO for signs and symptoms of infection (including osteomyelitis), new pain or tenderness, sores or ulcers involving the lower limbs, and discontinue STEGLATRO if these complications occur.

5.3 Volume Depletion

STEGLATRO can cause intravascular volume contraction which may sometimes manifest as symptomatic hypotension or acute transient changes in creatinine [see Adverse Reactions (6.1)]. There have been postmarketing reports of acute kidney injury, some requiring hospitalization and dialysis, in patients with type 2 diabetes mellitus receiving SGLT2 inhibitors, including STEGLATRO. Patients with impaired renal function (eGFR less than 60 mL/min/1.73 m^2) [see Use in Specific Populations (8.6)], elderly patients, patients with low systolic blood pressure, or patients on loop diuretics may be at increased risk for volume depletion or hypotension. Before initiating STEGLATRO in patients with one or more of these characteristics, assess volume status and renal function. In patients with volume depletion, correct this condition before initiating STEGLATRO. Monitor for signs and symptoms of volume depletion, and renal function after initiating therapy.

5.4 Urosepsis and Pyelonephritis

There have been postmarketing reports of serious urinary tract infections, including urosepsis and pyelonephritis, requiring hospitalization in patients receiving SGLT2 inhibitors. Treatment with SGLT2 inhibitors increases the risk for urinary tract infections. Evaluate patients for signs and symptoms of urinary tract infections and treat promptly, if indicated [see Adverse Reactions (6.1)].

5.5 Hypoglycemia with Concomitant Use with Insulin or Insulin Secretagogues

Insulin and insulin secretagogues (e.g., sulfonylurea) are known to cause hypoglycemia. STEGLATRO may increase the risk of hypoglycemia when used in combination with insulin or an insulin secretagogue [see Adverse Reactions (6.1)]. The risk of hypoglycemia may be lowered by a reduction in the dose of insulin or sulfonylurea (or other concomitantly administered insulin secretagogues). Inform patients using these medications concomitantly of this risk and educate them on the signs and symptoms of hypoglycemia.

5.6 Necrotizing Fasciitis of the Perineum (Fournier's Gangrene)

Reports of necrotizing fasciitis of the perineum (Fournier's Gangrene), a rare but serious and life-threatening necrotizing infection requiring urgent surgical intervention, have been identified in postmarketing surveillance in patients with diabetes mellitus receiving SGLT2 inhibitors, including STEGLATRO. Cases have been reported in females and males. Serious outcomes have included hospitalization, multiple surgeries, and death.

Patients treated with STEGLATRO presenting with pain or tenderness, erythema, or swelling in the genital or perineal area, along with fever or malaise, should be assessed for necrotizing fasciitis. If suspected, start treatment immediately with broad-spectrum antibiotics and, if necessary, surgical debridement. Discontinue STEGLATRO, closely monitor blood glucose levels, and provide appropriate alternative therapy for glycemic control.

5.7 Genital Mycotic Infections

STEGLATRO increases the risk of genital mycotic infections. Patients who have a history of genital mycotic infections or who are uncircumcised are more likely to develop genital mycotic infections [see Adverse Reactions (6.1)]. Monitor and treat appropriately.

6 ADVERSE REACTIONS

The following important adverse reactions are described elsewhere in the labeling:

- Diabetic Ketoacidosis in Patients with Type 1 Diabetes and Other Ketoacidosis [see Warnings and Precautions (5.1)]
- Lower Limb Amputation [see Warnings and Precautions (5.2)]
- Volume Depletion [see Warnings and Precautions (5.3)]
- Urosepsis and Pyelonephritis [see Warnings and Precautions (5.4)]
- Hypoglycemia with Concomitant Use with Insulin or Insulin Secretagogues [see Warnings and Precautions (5.5)]
- Necrotizing Fasciitis of the Perineum (Fournier's Gangrene) [see Warnings and Precautions (5.6)]
- Genital Mycotic Infections [see Warnings and Precautions (5.7)]

6.1 Clinical Trials Experience

Because clinical trials are conducted under widely varying conditions, adverse reaction rates observed in the clinical trials of a drug cannot be directly compared to rates in the clinical trials of another drug and may not reflect the rates observed in practice.

Pool of Placebo-Controlled Trials Evaluating STEGLATRO 5 and 15 mg

The data in Table 1 are derived from a pool of three 26-week, placebo-controlled trials. STEGLATRO was used as monotherapy in one trial and as add-on therapy in two trials [see Clinical Studies (14)]. These data reflect exposure of 1,029 patients to STEGLATRO with a mean exposure duration of approximately 25 weeks. Patients received STEGLATRO 5 mg (N=519), STEGLATRO 15 mg (N=510), or placebo (N=515) once daily. The mean age of the population was 57 years and 2% were older than 75 years of age. Fifty-three percent (53%) of the population was male and 73% were White, 15% were Asian, and 7% were Black or African American. At baseline the population had diabetes for an average of 7.5 years, had a mean HbA1c of 8.1%, and 19.4% had established microvascular complications of diabetes. Baseline renal function (mean eGFR 88.9 mL/min/1.73 m^2) was normal or mildly impaired in 97% of patients and moderately impaired in 3% of patients.

Table 1 shows common adverse reactions associated with the use of STEGLATRO. These adverse reactions were not present at baseline, occurred more commonly on STEGLATRO than on placebo, and occurred in at least 2% of patients treated with either STEGLATRO 5 mg or STEGLATRO 15 mg.

Table 1: Adverse Reactions Reported in ≥2% of Patients with Type 2 Diabetes Mellitus Treated with STEGLATRO [The three placebo-controlled studies included one monotherapy trial and two add-on combination trials with metformin HCl or with metformin HCl and sitagliptin.] and Greater than Placebo in Pooled Placebo-Controlled Clinical Studies of STEGLATRO Monotherapy or Combination Therapy
 | Number (%) of Patients
 | Placebo N = 515 | STEGLATRO 5 mg N = 519 | STEGLATRO 15 mg N = 510
Female genital mycotic infections [Includes: genital candidiasis, genital infection fungal, vaginal infection, vulvitis, vulvovaginal candidiasis, vulvovaginal mycotic infection, and vulvovaginitis. Percentages calculated with the number of female patients in each group as denominator: placebo (N=235), STEGLATRO 5 mg (N=252), STEGLATRO 15 mg (N=245).] | 3.0% | 9.1% | 12.2%
Male genital mycotic infections [Includes: balanitis candida, balanoposthitis, genital infection, and genital infection fungal. Percentages calculated with the number of male patients in each group as denominator: placebo (N=280), STEGLATRO 5 mg (N=267), STEGLATRO 15 mg (N=265).] | 0.4% | 3.7% | 4.2%
Urinary tract infections [Includes: cystitis, dysuria, streptococcal urinary tract infection, urethritis, urinary tract infection.] | 3.9% | 4.0% | 4.1%
Headache | 2.3% | 3.5% | 2.9%
Vaginal pruritus [Includes: vulvovaginal pruritus and pruritus genital. Percentages calculated with the number of female patients in each group as denominator: placebo (N=235), ertugliflozin 5 mg (N=252), ertugliflozin 15 mg (N=245).] | 0.4% | 2.8% | 2.4%
Increased urination [Includes: pollakiuria, micturition urgency, polyuria, urine output increased, and nocturia.] | 1.0% | 2.7% | 2.4%
Nasopharyngitis | 2.3% | 2.5% | 2.0%
Back pain | 2.3% | 1.7% | 2.5%
Weight decreased | 1.0% | 1.2% | 2.4%
Thirst [Includes: thirst, dry mouth, polydipsia, and dry throat.] | 0.6% | 2.7% | 1.4%

Volume Depletion

STEGLATRO causes an osmotic diuresis, which may lead to intravascular volume contraction and adverse reactions related to volume depletion, particularly in patients with impaired renal function (eGFR less than 60 mL/min/1.73 m^2). In patients with moderate renal impairment, adverse reactions related to volume depletion (e.g., dehydration, dizziness postural, presyncope, syncope, hypotension, and orthostatic hypotension) were reported in 0%, 4.4%, and 1.9% of patients treated with placebo, STEGLATRO 5 mg, and STEGLATRO 15 mg, respectively. STEGLATRO may also increase the risk of hypotension in other patients at risk for volume contraction [see Use in Specific Populations (8.5, 8.6)].

Hypoglycemia

The incidence of hypoglycemia by study is shown in Table 2.

Table 2: Incidence of Overall [Overall hypoglycemic events: plasma or capillary glucose of less than or equal to 70 mg/dL.] and Severe [Severe hypoglycemic events: required assistance, lost consciousness, or experienced a seizure regardless of blood glucose.] Hypoglycemia in Placebo-Controlled Clinical Studies in Patients with Type 2 Diabetes Mellitus
Monotherapy (26 weeks) | Placebo (N = 153) | STEGLATRO 5 mg (N =156) | STEGLATRO 15 mg (N = 152)
Overall [N (%)] | 1 (0.7) | 4 (2.6) | 4 (2.6)
Severe [N (%)] | 0 (0.0) | 0 (0.0) | 2 (1.3)
Add-on Combination Therapy with Metformin HCl (26 weeks) | Placebo (N = 209) | STEGLATRO 5 mg (N = 207) | STEGLATRO 15 mg (N = 205)
Overall [N (%)] | 9 (4.3) | 15 (7.2) | 16 (7.8)
Severe [N (%)] | 1 (0.5) | 1 (0.5) | 0 (0.0)
Add-on Combination Therapy with Metformin HCl and Sitagliptin (26 weeks) | Placebo (N = 153) | STEGLATRO 5 mg (N = 156) | STEGLATRO 15 mg (N = 153)
Overall [N (%)] | 5 (3.3) | 7 (4.5) | 3 (2.0)
Severe [N (%)] | 1 (0.7) | 1 (0.6) | 0 (0.0)
In Combination with Insulin and/or an Insulin Secretagogue in Patients with Moderate Renal Impairment (26 weeks) | Placebo (N = 133) | STEGLATRO 5 mg (N = 148) | STEGLATRO 15 mg (N = 143)
Overall [N (%)] | 48 (36.1) | 53 (35.8) | 39 (27.3)
Severe [N (%)] | 3 (2.3) | 5 (3.4) | 3 (2.1)
Add-on Combination with Insulin with or without Metformin HCl (18 weeks) | Placebo (N = 347) | STEGLATRO 5 mg (N = 348) | STEGLATRO 15 mg (N = 370)
Overall [N (%)] | 130 (37.5) | 137 (39.4) | 144 (38.9)
Severe [N (%)] | 12 (3.5) | 13 (3.7) | 19 (5.1)
Add-on Combination with a Sulfonylurea (18 weeks) | Placebo (N =48) | STEGLATRO 5 mg (N =55) | STEGLATRO 15 mg (N =54)
Overall [N (%)] | 2 (4.2) | 4 (7.3) | 5 (9.3)
Severe [N (%)] | 0 (0.0) | 0 (0.0) | 0 (0.0)
Add-on Combination with Metformin HCl and a Sulfonylurea (18 weeks) | Placebo (N = 117) | STEGLATRO 5 mg (N = 100) | STEGLATRO 15 mg (N = 113)
Overall [N (%)] | 17 (14.5) | 20 (20.0) | 30 (26.5)
Severe [N (%)] | 1 (0.9) | 2 (2.0) | 2 (1.8)

Lower Limb Amputation

In a long-term cardiovascular outcomes study [see Clinical Studies (14.2)], in patients with type 2 diabetes mellitus and established cardiovascular disease, the occurrence of non-traumatic lower limb amputations was reported with event rates of 4.7, 5.7, and 6.0 events per 1,000 patient-years in the placebo, STEGLATRO 5 mg, and STEGLATRO 15 mg treatment arms, respectively.

Across seven STEGLATRO clinical trials, non-traumatic lower limb amputations were reported in 1 (0.1%) patient in the comparator group, 3 (0.2%) patients in the STEGLATRO 5 mg group, and 8 (0.5%) patients in the STEGLATRO 15 mg group.

Genital Mycotic Infections

In the pool of three placebo-controlled clinical trials, the incidence of female genital mycotic infections (e.g., genital candidiasis, genital infection fungal, vaginal infection, vulvitis, vulvovaginal candidiasis, vulvovaginal mycotic infection, vulvovaginitis) occurred in 3%, 9.1%, and 12.2% of females treated with placebo, STEGLATRO 5 mg, and STEGLATRO 15 mg, respectively (see Table 1). In females, discontinuation due to genital mycotic infections occurred in 0% and 0.6% of patients treated with placebo and STEGLATRO, respectively.

In the same pool, male genital mycotic infections (e.g., balanitis candida, balanoposthitis, genital infection, genital infection fungal) occurred in 0.4%, 3.7%, and 4.2% of males treated with placebo, STEGLATRO 5 mg, and STEGLATRO 15 mg, respectively (see Table 1). Male genital mycotic infections occurred more commonly in uncircumcised males. In males, discontinuations due to genital mycotic infections occurred in 0% and 0.2% of patients treated with placebo and STEGLATRO, respectively. Phimosis was reported in 8 of 1729 (0.5%) male ertugliflozin-treated patients, of which four required circumcision.

Urinary Tract Infections

In VERTIS CV, urinary tract infections (e.g., urinary tract infection, cystitis, dysuria) occurred in 10.2%, 12.2% and 12.0% of patients treated with placebo, STEGLATRO 5 mg and STEGLATRO 15 mg, respectively. The incidences of serious urinary tract infections were 0.8%, 0.9% and 0.4% with placebo, STEGLATRO 5 mg and STEGLATRO 15 mg, respectively.

Laboratory Tests

Changes in Serum Creatinine and eGFR

Initiation of STEGLATRO causes an increase in serum creatinine and decrease in eGFR within weeks of starting therapy and then these changes stabilize. In a study of patients with moderate renal impairment, larger mean changes were observed. In a long-term cardiovascular outcomes trial, an initial increase in serum creatinine and a decrease in eGFR within weeks of starting therapy was observed (at Week 6 eGFR changes of -2.7, -3.8 and -0.4 mL/min/1.73 m^2 in the STEGLATRO 5 mg, STEGLATRO 15 mg and placebo arms, respectively). The initial decline was followed by a recovery toward baseline to Week 52 (eGFR change from baseline of - 0.4, - 1.1 and - 0.2 mL/min/1.73 m^2 in STEGLATRO 5 mg, STEGLATRO 15 mg, and placebo arms, respectively). Acute hemodynamic changes may play a role in the early renal function changes observed with STEGLATRO since they are reversed after treatment discontinuation.

Increases in Low-Density Lipoprotein Cholesterol (LDL-C)

In the pool of three placebo-controlled trials, dose-related increases in LDL-C were observed in patients treated with STEGLATRO. Mean percent changes from baseline to Week 26 in LDL-C relative to placebo were 2.6% and 5.4% with STEGLATRO 5 mg and STEGLATRO 15 mg, respectively. The range of mean baseline LDL-C was 96.6 to 97.7 mg/dL across treatment groups.

Increases in Hemoglobin

In the pool of three placebo-controlled trials, mean changes (percent changes) from baseline to Week 26 in hemoglobin were -0.21 g/dL (-1.4%) with placebo, 0.46 g/dL (3.5%) with STEGLATRO 5 mg, and 0.48 g/dL (3.5%) with STEGLATRO 15 mg. The range of mean baseline hemoglobin was 13.90 to 14.00 g/dL across treatment groups. At the end of treatment, 0.0%, 0.2%, and 0.4% of patients treated with placebo, STEGLATRO 5 mg, and STEGLATRO 15 mg, respectively, had a hemoglobin increase greater than 2 g/dL and above the upper limit of normal.

Increases in Serum Phosphate

In the pool of three placebo-controlled trials, mean changes (percent changes) from baseline in serum phosphate were 0.04 mg/dL (1.9%) with placebo, 0.21 mg/dL (6.8%) with STEGLATRO 5 mg, and 0.26 mg/dL (8.5%) with STEGLATRO 15 mg. The range of mean baseline serum phosphate was 3.53 to 3.54 mg/dL across treatment groups. In a clinical trial of patients with moderate renal impairment, mean changes (percent changes) from baseline at Week 26 in serum phosphate were -0.01 mg/dL (0.8%) with placebo, 0.29 mg/dL (9.7%) with STEGLATRO 5 mg, and 0.24 mg/dL (7.8%) with STEGLATRO 15 mg.

6.2 Postmarketing Experience

Additional adverse reactions have been identified during postapproval use of STEGLATRO. Because these reactions are reported voluntarily from a population of uncertain size, it is generally not possible to reliably estimate their frequency or establish a causal relationship to drug exposure.

- Infections: necrotizing fasciitis of the perineum (Fournier's Gangrene)
- Skin and Subcutaneous Tissue Disorders: angioedema, rash

7 DRUG INTERACTIONS

Table 3: Clinically Significant Drug Interactions with STEGLATRO
Insulin or Insulin Secretagogues
Clinical Impact: | The risk of hypoglycemia is increased when STEGLATRO is used in combination with insulin or an insulin secretagogue.
Intervention: | A lower dose of insulin or insulin secretagogue may be required to minimize the risk of hypoglycemia when used in combination with STEGLATRO.
Lithium
Clinical Impact: | Concomitant use of an SGLT2 inhibitor with lithium may decrease serum lithium concentrations.
Intervention: | Monitor serum lithium concentration more frequently during STEGLATRO initiation and dosage changes.
Positive Urine Glucose Test
Clinical Impact: | SGLT2 inhibitors increase urinary glucose excretion and will lead to positive urine glucose tests.
Intervention: | Monitoring glycemic control with urine glucose tests is not recommended in patients taking SGLT2 inhibitors. Use alternative methods to monitor glycemic control.
Interference with 1,5-anhydroglucitol (1,5-AG) Assay
Clinical Impact: | Measurements of 1,5-AG are unreliable in assessing glycemic control in patients taking SGLT2 inhibitors.
Intervention: | Monitoring glycemic control with 1,5-AG assay is not recommended. Use alternative methods to monitor glycemic control.

8 USE IN SPECIFIC POPULATIONS

8.1 Pregnancy

Risk Summary

Based on animal data showing adverse renal effects, STEGLATRO is not recommended during the second and third trimesters of pregnancy.

The limited available data with STEGLATRO in pregnant women are not sufficient to determine a drug-associated risk of adverse developmental outcomes. There are risks to the mother and fetus associated with poorly controlled diabetes in pregnancy (see Clinical Considerations).

In animal studies, adverse renal changes were observed in rats when ertugliflozin was administered during a period of renal development corresponding to the late second and third trimesters of human pregnancy. Doses approximately 13 times the maximum clinical dose caused renal pelvic and tubule dilatations and renal mineralization that were not fully reversible. There was no evidence of fetal harm in rats or rabbits at exposures of ertugliflozin approximately 300 times higher than the maximal clinical dose of 15 mg/day when administered during organogenesis (see Data).

The estimated background risk of major birth defects is 6-10% in women with pre-gestational diabetes with a HbA1c >7 and has been reported to be as high as 20-25% in women with HbA1c >10. The estimated background risk of miscarriage for the indicated population is unknown. In the U.S. general population, the estimated background risk of major birth defects and miscarriage in clinically recognized pregnancies is 2-4% and 15-20%, respectively.

Clinical Considerations

Disease-Associated Maternal and/or Embryo/Fetal Risk

Poorly controlled diabetes in pregnancy increases the maternal risk for diabetic ketoacidosis, pre-eclampsia, spontaneous abortions, preterm delivery, and delivery complications. Poorly controlled diabetes increases the fetal risk for major birth defects, stillbirth, and macrosomia related morbidity.

Data

Animal Data

When ertugliflozin was orally administered to juvenile rats from PND 21 to PND 90, increased kidney weight, renal tubule and renal pelvis dilatation, and renal mineralization occurred at doses greater than or equal to 5 mg/kg (13-fold human exposures, based on AUC). These effects occurred with drug exposure during periods of renal development in rats that correspond to the late second and third trimester of human renal development, and did not fully reverse within a 1-month recovery period.

In embryo-fetal development studies, ertugliflozin (50, 100 and 250 mg/kg/day) was administered orally to rats on gestation days 6 to 17 and to rabbits on gestation days 7 to 19. Ertugliflozin did not adversely affect developmental outcomes in rats and rabbits at maternal exposures that were approximately 300 times the human exposure at the maximum clinical dose of 15 mg/day, based on AUC. A maternally toxic dose (250 mg/kg/day) in rats (707 times the clinical dose), was associated with reduced fetal viability, and a higher incidence of a visceral malformation (membranous ventricular septal defect). In the pre- and post-natal development study in pregnant rats, ertugliflozin was administered to the dams from gestation day 6 through lactation day 21 (weaning). Decreased post-natal growth (weight gain) was observed at maternal doses ≥100 mg/kg/day (greater than or equal to 331 times the human exposure at the maximum clinical dose of 15 mg/day, based on AUC).

8.2 Lactation

Risk Summary

There is no information regarding the presence of STEGLATRO in human milk, the effects on the breastfed infant, or the effects on milk production. Ertugliflozin is present in the milk of lactating rats (see Data). Since human kidney maturation occurs in utero and during the first 2 years of life when lactational exposure may occur, there may be risk to the developing human kidney. Because of the potential for serious adverse reactions in a breastfed infant, advise women that the use of STEGLATRO is not recommended while breastfeeding.

Data

The lacteal excretion of radiolabeled ertugliflozin in lactating rats was evaluated 10 to 12 days after parturition. Ertugliflozin derived radioactivity exposure in milk and plasma were similar, with a milk/plasma ratio of 1.07, based on AUC. Juvenile rats directly exposed to STEGLATRO during a developmental period corresponding to human kidney maturation were associated with a risk to the developing kidney (persistent increased organ weight, renal mineralization, and renal pelvic and tubular dilatations).

8.4 Pediatric Use

Safety and effectiveness of STEGLATRO in pediatric patients under 18 years of age have not been established.

8.5 Geriatric Use

No dosage adjustment of STEGLATRO is recommended based on age. In STEGLATRO clinical trials, a total of 876 (25.7%) patients treated with STEGLATRO were 65 years and older, and 152 (4.5%) patients treated with STEGLATRO were 75 years and older. Patients 65 years and older had a higher incidence of adverse reactions related to volume depletion compared to younger patients; events were reported in 1.1%, 2.2%, and 2.6% of patients treated with comparator, STEGLATRO 5 mg, and STEGLATRO 15 mg, respectively [see Warnings and Precautions (5.3) and Adverse Reactions (6.1)].

In VERTIS CV, a total of 2780 (50.5%) patients treated with STEGLATRO were 65 years and older, and 595 (10.8%) patients treated with STEGLATRO were 75 years and older. Safety and efficacy were generally similar for patients age 65 years and older compared to patients younger than 65.

8.6 Renal Impairment

A 26-week placebo-controlled study of 313 patients with Stage 3 Chronic Kidney Disease (eGFR ≥30 to less than 60 mL/min/1.73 m^2) treated with STEGLATRO did not demonstrate improvement in glycemic control.

In the VERTIS CV study, there were 1370 patients (25%) with an eGFR ≥90 mL/min/1.73 m^2, 2929 patients (53%) with an eGFR of ≥60 to less than 90 mL/min/1.73 m^2, 879 patients (16%) with an eGFR of ≥45 to less than 60 mL/min/1.73 m^2, and 299 patients (5%) with eGFR of 30 to <45 mL/min/1.73 m^2 treated with STEGLATRO. Similar effects on glycemic control at Week 18 were observed in patients treated with STEGLATRO in each eGFR subgroup and also in the overall patient population.

No dosage adjustment is needed in patients with eGFR ≥45 mL/min/1.73 m^2.

8.7 Hepatic Impairment

No dosage adjustment of STEGLATRO is necessary in patients with mild or moderate hepatic impairment. Ertugliflozin has not been studied in patients with severe hepatic impairment and is not recommended for use in this patient population [see Clinical Pharmacology (12.3)].

10 OVERDOSAGE

In the event of an overdose with STEGLATRO, contact the Poison Help line (1-800-222-1222) or a medical toxicologist for additional overdosage management recommendations. Employ the usual supportive measures as dictated by the patient's clinical status. Removal of ertugliflozin by hemodialysis has not been studied.

11 DESCRIPTION

STEGLATRO (ertugliflozin) tablets for oral use contain ertugliflozin L-pyroglutamic acid, a SGLT2 inhibitor.

The chemical name of ertugliflozin L-pyroglutamic acid is (1S,2S,3S,4R,5S)-5-(4-chloro-3-(4-ethoxybenzyl)phenyl)-1-(hydroxymethyl)-6,8-dioxabicyclo[3.2.1]octane-2,3,4-triol, compound with (2S)-5-oxopyrrolidine-2-carboxylic acid. The molecular formula is C27H32ClNO10 and the molecular weight is 566.00.

The chemical structure is:

Ertugliflozin L-pyroglutamic acid is a white to off-white powder that is soluble in ethyl alcohol and acetone, slightly soluble in ethyl acetate and acetonitrile and very slightly soluble in water.

STEGLATRO is supplied as film-coated tablets, containing 6.48 or 19.43 mg of ertugliflozin L-pyroglutamic acid, which is equivalent to 5 and 15 mg of ertugliflozin.

Inactive ingredients are microcrystalline cellulose, lactose monohydrate, sodium starch glycolate, and magnesium stearate.

The film coating contains: hypromellose, lactose monohydrate, macrogol, triacetin, titanium dioxide and iron oxide red.

12 CLINICAL PHARMACOLOGY

12.1 Mechanism of Action

SGLT2 is the predominant transporter responsible for reabsorption of glucose from the glomerular filtrate back into the circulation. Ertugliflozin is an inhibitor of SGLT2. By inhibiting SGLT2, ertugliflozin reduces renal reabsorption of filtered glucose and lowers the renal threshold for glucose, and thereby increases urinary glucose excretion.

12.2 Pharmacodynamics

Urinary Glucose Excretion and Urinary Volume

Dose-dependent increases in the amount of glucose excreted in urine were observed in healthy subjects and in patients with type 2 diabetes mellitus following single- and multiple-dose administration of ertugliflozin. Dose-response modeling indicates that ertugliflozin 5 mg and 15 mg result in near maximal urinary glucose excretion (UGE). Enhanced UGE is maintained after multiple-dose administration. UGE with ertugliflozin also results in increases in urinary volume.

Cardiac Electrophysiology

The effect of STEGLATRO on QTc interval was evaluated in a Phase 1 randomized, placebo- and positive-controlled 3-period crossover study in 42 healthy subjects. At 6.7 times the therapeutic exposures with maximum recommended dose, STEGLATRO does not prolong QTc to any clinically relevant extent.

12.3 Pharmacokinetics

The pharmacokinetics of ertugliflozin are similar in healthy subjects and patients with type 2 diabetes mellitus. The steady state mean plasma AUC and Cmax were 398 ng∙hr/mL and 81.3 ng/mL, respectively, with 5 mg ertugliflozin once-daily treatment, and 1,193 ng∙hr/mL and 268 ng/mL, respectively, with 15 mg ertugliflozin once-daily treatment. Steady-state is reached after 4 to 6 days of once-daily dosing with ertugliflozin. Ertugliflozin does not exhibit time-dependent pharmacokinetics and accumulates in plasma up to 10-40% following multiple dosing.

Absorption

Following single-dose oral administration of 5 mg and 15 mg of ertugliflozin, peak plasma concentrations (median Tmax) of ertugliflozin occur at 1 hour postdose under fasted conditions. Plasma Cmax and AUC of ertugliflozin increase in a dose-proportional manner following single doses from 0.5 mg (0.1 times the lowest recommended dose) to 300 mg (20 times the highest recommended dose) and following multiple doses from 1 mg (0.2 times the lowest recommended dose) to 100 mg (6.7 times the highest recommended dose). The absolute oral bioavailability of ertugliflozin following administration of a 15 mg dose is approximately 100%.

Effect of Food

Administration of STEGLATRO with a high-fat and high-calorie meal decreases ertugliflozin Cmax by 29% and prolongs Tmax by 1 hour, but does not alter AUC as compared with the fasted state. The observed effect of food on ertugliflozin pharmacokinetics is not considered clinically relevant, and ertugliflozin may be administered with or without food. In Phase 3 clinical trials, STEGLATRO was administered without regard to meals.

Distribution

The mean steady-state volume of distribution of ertugliflozin following an intravenous dose is 85.5 L. Plasma protein binding of ertugliflozin is 93.6% and is independent of ertugliflozin plasma concentrations. Plasma protein binding is not meaningfully altered in patients with renal or hepatic impairment. The blood-to-plasma concentration ratio of ertugliflozin is 0.66.

Elimination

Metabolism

Metabolism is the primary clearance mechanism for ertugliflozin. The major metabolic pathway for ertugliflozin is UGT1A9 and UGT2B7-mediated O-glucuronidation to two glucuronides that are pharmacologically inactive at clinically relevant concentrations. CYP-mediated (oxidative) metabolism of ertugliflozin is minimal (12%).

Excretion

The mean systemic plasma clearance following an intravenous 100 µg dose was 11.2 L/hr. The mean elimination half-life in type 2 diabetic patients with normal renal function was estimated to be 16.6 hours based on the population pharmacokinetic analysis. Following administration of an oral [^14C]-ertugliflozin solution to healthy subjects, approximately 40.9% and 50.2% of the drug-related radioactivity was eliminated in feces and urine, respectively. Only 1.5% of the administered dose was excreted as unchanged ertugliflozin in urine and 33.8% as unchanged ertugliflozin in feces, which is likely due to biliary excretion of glucuronide metabolites and subsequent hydrolysis to parent.

Specific Populations

Patients with Renal Impairment

In a clinical pharmacology study in patients with type 2 diabetes mellitus and mild, moderate, or severe renal impairment (as determined by eGFR), following a single-dose administration of 15 mg STEGLATRO, the mean increases in AUC of ertugliflozin were 1.6-, 1.7-, and 1.6-fold, respectively, for mild, moderate and severe renally impaired patients, compared to subjects with normal renal function. These increases in ertugliflozin AUC are not considered clinically meaningful. The 24-hour urinary glucose excretion declined with increasing severity of renal impairment [see Warnings and Precautions (5.3) and Use in Specific Populations (8.6)]. The plasma protein binding of ertugliflozin was unaffected in patients with renal impairment.

Patients with Hepatic Impairment

Moderate hepatic impairment (based on the Child-Pugh classification) did not result in an increase in exposure of ertugliflozin. The AUC of ertugliflozin decreased by approximately 13%, and Cmax decreased by approximately 21% compared to subjects with normal hepatic function. This decrease in ertugliflozin exposure is not considered clinically meaningful. There is no clinical experience in patients with Child-Pugh class C (severe) hepatic impairment. The plasma protein binding of ertugliflozin was unaffected in patients with moderate hepatic impairment [see Use in Specific Populations (8.7)].

Effects of Age, Body Weight, Gender, and Race

Based on a population pharmacokinetic analysis, age, body weight, gender, and race do not have a clinically meaningful effect on the pharmacokinetics of ertugliflozin.

Drug Interaction Studies

In Vitro Assessment of Drug Interactions

In in vitro studies, ertugliflozin and ertugliflozin glucuronides did not inhibit CYP450 isoenzymes (CYPs) 1A2, 2C9, 2C19, 2C8, 2B6, 2D6, or 3A4, and did not induce CYPs 1A2, 2B6, or 3A4. Ertugliflozin was not a time-dependent inhibitor of CYP3A in vitro. Ertugliflozin did not inhibit UGT1A6, 1A9, or 2B7 in vitro and was a weak inhibitor (IC50 >39 µM) of UGT1A1 and 1A4. Ertugliflozin glucuronides did not inhibit UGT1A1, 1A4, 1A6, 1A9, or 2B7 in vitro. Overall, ertugliflozin is unlikely to affect the pharmacokinetics of drugs eliminated by these enzymes. Ertugliflozin is a substrate of P-glycoprotein (P-gp) and breast cancer resistance protein (BCRP) transporters and is not a substrate of organic anion transporters (OAT1, OAT3), organic cation transporters (OCT1, OCT2), or organic anion transporting polypeptides (OATP1B1, OATP1B3). Ertugliflozin or ertugliflozin glucuronides do not meaningfully inhibit P-gp, OCT2, OAT1, or OAT3 transporters, or transporting polypeptides OATP1B1 and OATP1B3, at clinically relevant concentrations. Overall, ertugliflozin is unlikely to affect the pharmacokinetics of concurrently administered medications that are substrates of these transporters.

In Vivo Assessment of Drug Interactions

No dose adjustment of STEGLATRO is recommended when coadministered with commonly prescribed medicinal products. Ertugliflozin pharmacokinetics were similar with and without coadministration of metformin, glimepiride, sitagliptin, and simvastatin in healthy subjects (see Figure 1). Coadministration of ertugliflozin with multiple doses of 600 mg once-daily rifampin (an inducer of UGT and CYP enzymes) resulted in approximately 39% and 15% mean reductions in ertugliflozin AUC and Cmax, respectively, relative to ertugliflozin administered alone. These changes in exposure are not considered clinically relevant. Ertugliflozin had no clinically relevant effect on the pharmacokinetics of metformin, glimepiride, sitagliptin, and simvastatin when coadministered in healthy subjects (see Figure 2). Physiologically-based PK (PBPK) modeling suggests that coadministration of mefenamic acid (UGT inhibitor) may increase the AUC and Cmax of ertugliflozin by 1.51- and 1.19-fold, respectively. These predicted changes in exposure are not considered clinically relevant.

Figure 1: Effects of Other Drugs on the Pharmacokinetics of Ertugliflozin

Figure 2: Effects of Ertugliflozin on the Pharmacokinetics of Other Drugs

13 NONCLINICAL TOXICOLOGY

13.1 Carcinogenesis, Mutagenesis, Impairment of Fertility

Carcinogenesis

Carcinogenicity was evaluated in CD-1 mice and Sprague-Dawley rats. In the mouse study, ertugliflozin was administered by oral gavage at doses of 5, 15, and 40 mg/kg/day for up to 97 weeks in males and 102 weeks in females. There were no ertugliflozin-related neoplastic findings at doses up to 40 mg/kg/day (approximately 50 times human exposure at the maximum recommended human dose [MRHD] of 15 mg/day based on AUC). In the rat study, ertugliflozin was administered by oral gavage at doses of 1.5, 5, and 15 mg/kg/day for up to 92 weeks in females and 104 weeks in males. Ertugliflozin-related neoplastic findings included an increased incidence of adrenal medullary pheochromocytoma (PCC) in male rats at 15 mg/kg/day. Although the molecular mechanism remains unknown, this finding may be related to carbohydrate malabsorption leading to altered calcium homeostasis, which has been associated with PCC development in rats and has unclear relevancy to human risk. The no-observed-effect level (NOEL) for neoplasia was 5 mg/kg/day (approximately 16 times human exposure at the MRHD of 15 mg/day, based on AUC).

Mutagenesis

Ertugliflozin was not mutagenic or clastogenic with or without metabolic activation in the microbial reverse mutation, in vitro cytogenetic (human lymphocytes), and in vivo rat micronucleus assays.

Impairment of Fertility

In the rat fertility and embryonic development study, male and female rats were administered ertugliflozin at 5, 25, and 250 mg/kg/day. No effects on fertility were observed at 250 mg/kg/day (approximately 480 and 570 times male and female human exposures, respectively, at the MRHD of 15 mg/day based on AUC comparison).

14 CLINICAL STUDIES

14.1 Glycemic Control Trials in Patients with Type 2 Diabetes Mellitus

STEGLATRO has been studied as monotherapy and in combination with metformin HCl, sitagliptin, a sulfonylurea, insulin (with or without metformin HCl), metformin HCl plus sitagliptin, metformin HCl plus a sulfonylurea and compared to a sulfonylurea (glimepiride). STEGLATRO has also been studied in patients with type 2 diabetes mellitus and moderate renal impairment.

In patients with type 2 diabetes mellitus treatment with STEGLATRO reduced hemoglobin A1c (HbA1c) compared to placebo. Reduction in HbA1c was generally similar across subgroups defined by age, sex, race, geographic region, baseline body mass index (BMI), and duration of type 2 diabetes mellitus.

Monotherapy

A total of 461 patients with type 2 diabetes mellitus inadequately controlled (HbA1c between 7% and 10.5%) on diet and exercise participated in a randomized, double-blind, multi-center, 26-week, placebo-controlled study (NCT01958671) to evaluate the efficacy and safety of STEGLATRO monotherapy. These patients, who were either treatment naïve or not receiving any background antihyperglycemic treatment ≥8 weeks, entered a 2-week, single-blind, placebo run-in period and were randomized to placebo, STEGLATRO 5 mg, or STEGLATRO 15 mg, administered once daily.

At Week 26, treatment with STEGLATRO at 5 mg or 15 mg orally once daily provided statistically significant reductions in HbA1c compared to placebo. STEGLATRO also resulted in a greater proportion of patients achieving an HbA1c <7% compared with placebo (see Table 4 and Figure 3).

Table 4: Results at Week 26 from a Placebo-Controlled Monotherapy Study of STEGLATRO in Patients with Type 2 Diabetes Mellitus [N includes all randomized and treated patients with a baseline measurement of the outcome variable. At Week 26, the primary HbA1c endpoint was missing for 23%, 11%, and 16% of patients, and during the trial, rescue medication was initiated by 25%, 2%, and 3% of patients randomized to placebo, STEGLATRO 5 mg, and STEGLATRO 15 mg, respectively. Missing Week 26 measurements were imputed using multiple imputation with a mean equal to the baseline value of the patient. Results include measurements collected after initiation of rescue medication. For those patients who did not receive rescue medication and had values measured at 26 weeks, the mean changes from baseline for HbA1c were -0.1%, -0.8%, and -1.0% for placebo, STEGLATRO 5 mg, and STEGLATRO 15 mg, respectively.]
 | Placebo | STEGLATRO 5 mg | STEGLATRO 15 mg
HbA1c (%) | N = 153 | N = 155 | N = 151
Baseline (mean) | 8.1 | 8.2 | 8.4
Change from baseline (LS mean [Intent-to-treat analysis using ANCOVA adjusted for baseline value, prior antihyperglycemic medication, and baseline eGFR.]) | -0.2 | -0.7 | -0.8
Difference from placebo (LS mean, 95% CI) |  | -0.6 [p<0.001 compared to placebo.] (-0.8, -0.4) | -0.7 (-0.9, -0.4)
Patients [N (%)] with HbA1c <7% | 26 (16.9) | 47 (30.1) | 59 (38.8)
FPG (mg/dL) | N = 150 | N = 151 | N = 149
Baseline (mean) | 180.2 | 180.9 | 179.1
Change from baseline (LS mean) | -11.6 | -31.0 | -36.4
Difference from placebo (LS mean, 95% CI) |  | -19.4 (-27.6, -11.2) | -24.8 (-33.2, -16.4)

The mean baseline body weight was 94.2 kg, 94.0 kg, and 90.6 kg in the placebo, STEGLATRO 5 mg, and STEGLATRO 15 mg groups, respectively. The mean changes from baseline to Week 26 were -1.0 kg, -3.0 kg, and -3.1 kg in the placebo, STEGLATRO 5 mg, and STEGLATRO 15 mg groups, respectively. The difference from placebo (95% CI) for STEGLATRO 5 mg was -2.0 kg (-2.8, -1.2) and for STEGLATRO 15 mg was -2.1 kg (-2.9, -1.3).

Figure 3: HbA1c (%) Change Over Time in a 26-Week Placebo-Controlled Monotherapy Study of STEGLATRO in Patients with Type 2 Diabetes Mellitus [Data to the left of the vertical line are observed means (non-model-based) excluding values occurring post glycemic rescue. Data to the right of the vertical line represent the final Week 26 data, including all values regardless of use of glycemic rescue medication and use of study drug, with missing Week 26 values imputed using multiple imputation (26-MI) with a mean equal to the baseline value of the patient (see Table 4).]

Combination Therapy

Add-on Combination Therapy with Metformin HCl

A total of 621 patients with type 2 diabetes mellitus inadequately controlled (HbA1c between 7% and 10.5%) on metformin HCl monotherapy (≥1,500 mg/day for ≥8 weeks) participated in a randomized, double-blind, multi-center, 26-week, placebo-controlled study (NCT02033889) to evaluate the efficacy and safety of STEGLATRO in combination with metformin HCl. Patients entered a 2-week, single-blind, placebo run-in, and were randomized to placebo, STEGLATRO 5 mg, or STEGLATRO 15 mg administered once daily in addition to continuation of background metformin HCl therapy.

At Week 26, treatment with STEGLATRO at 5 mg or 15 mg orally once daily provided statistically significant reductions in HbA1c compared to placebo. STEGLATRO also resulted in a greater proportion of patients achieving an HbA1c <7% compared to placebo (see Table 5).

Table 5: Results at Week 26 from a Placebo-Controlled Study for STEGLATRO Used in Combination with Metformin HCl in Patients with Type 2 Diabetes Mellitus [N includes all randomized and treated patients with a baseline measurement of the outcome variable. At Week 26, the primary HbA1c endpoint was missing for 12%, 6%, and 9% of patients, and during the trial, rescue medication was initiated by 18%, 3%, and 1% of patients randomized to placebo, STEGLATRO 5 mg, and STEGLATRO 15 mg, respectively. Missing Week 26 measurements were imputed using multiple imputation with a mean equal to the baseline value of the patient. Results include measurements collected after initiation of rescue medication. For those patients who did not receive rescue medication and had values measured at 26 weeks, the mean changes from baseline for HbA1c were -0.2%, -0.7%, and -1.0% for placebo, STEGLATRO 5 mg, and STEGLATRO 15 mg, respectively.]
 | Placebo | STEGLATRO 5 mg | STEGLATRO 15 mg
HbA1c (%) | N = 207 | N = 205 | N = 201
Baseline (mean) | 8.2 | 8.1 | 8.1
Change from baseline (LS mean [Intent-to-treat analysis using ANCOVA adjusted for baseline value, prior antihyperglycemic medication, menopausal status and baseline eGFR.]) | -0.2 | -0.7 | -0.9
Difference from placebo (LS mean, 95% CI) |  | -0.5 [p<0.001 compared to placebo.] (-0.7, -0.4) | -0.7 (-0.9, -0.5)
Patients [N (%)] with HbA1c <7% | 38 (18.4) | 74 (36.3) | 87 (43.3)
FPG (mg/dL) | N = 202 | N = 199 | N = 201
Baseline (mean) | 169.1 | 168.1 | 167.9
Change from baseline (LS mean) | -8.7 | -30.3 | -40.9
Difference from placebo (LS mean, 95% CI) |  | -21.6 (-27.8, -15.5) | -32.3 (-38.5, -26.0)

The mean baseline body weight was 84.5 kg, 84.9 kg, and 85.3 kg in the placebo, STEGLATRO 5 mg, and STEGLATRO 15 mg groups, respectively. The mean changes from baseline to Week 26 were -1.4 kg, -3.2 kg, and -3.0 kg in the placebo, STEGLATRO 5 mg, and STEGLATRO 15 mg groups, respectively. The difference from placebo (95% CI) for STEGLATRO 5 mg was -1.8 kg (-2.4, -1.2) and for STEGLATRO 15 mg was -1.7 kg (-2.2, -1.1).

The mean baseline systolic blood pressure was 129.3 mmHg, 130.5 mmHg, and 130.2 mmHg in the placebo, STEGLATRO 5 mg, and STEGLATRO 15 mg groups, respectively. The mean changes from baseline to Week 26 were -1.8 mmHg, -5.1 mmHg, and -5.7 mmHg in the placebo, STEGLATRO 5 mg, and STEGLATRO 15 mg groups, respectively. The difference from placebo (95% CI) for STEGLATRO 5 mg was -3.3 mmHg (-5.6, -1.1) and for STEGLATRO 15 mg was -3.8 mmHg (-6.1, -1.5).

Active Controlled Study versus Glimepiride as Add-on Combination Therapy with Metformin HCl

A total of 1,326 patients with type 2 diabetes mellitus inadequately controlled (HbA1c between 7% and 9%) on metformin HCl monotherapy participated in a randomized, double-blind, multi-center, 52-week, active comparator controlled study (NCT01999218) to evaluate the efficacy and safety of STEGLATRO in combination with metformin HCl. These patients, who were receiving metformin HCl monotherapy (≥1,500 mg/day for ≥8 weeks), entered a 2-week, single-blind, placebo run-in period and were randomized to glimepiride, STEGLATRO 5 mg, or STEGLATRO 15 mg administered orally once daily in addition to continuation of background metformin HCl therapy. Glimepiride was initiated at 1 mg/day and titrated up to a maximum dose of 6 or 8 mg/day (depending on maximum approved dose in each country) or a maximum tolerated dose or down-titrated to avoid or manage hypoglycemia. The mean daily dose of glimepiride was 3.0 mg.

STEGLATRO 15 mg was non-inferior to glimepiride after 52 weeks of treatment. (See Table 6.)

Table 6: Results at Week 52 from an Active-Controlled Study Comparing STEGLATRO to Glimepiride as Add-on Therapy in Patients with Type 2 Diabetes Mellitus Inadequately Controlled on Metformin HCl [N includes all randomized and treated patients with a baseline measurement of the outcome variable. At Week 52, the primary HbA1c endpoint was missing for 15%, 20%, and 16% of patients and during the trial, rescue medication was initiated by 3%, 6%, and 4% of patients randomized to glimepiride, STEGLATRO 5 mg, and STEGLATRO 15 mg, respectively. Missing Week 52 measurements were imputed using multiple imputation with a mean equal to the baseline value of the patient. Results include measurements collected after initiation of rescue medication. For those patients who did not receive rescue medication and had values measured at 52 weeks, the mean changes from baseline for HbA1c were -0.8%, -0.6%, and -0.7% for glimepiride, STEGLATRO 5 mg, and STEGLATRO 15 mg, respectively.]
 | Glimepiride | STEGLATRO 5 mg | STEGLATRO 15 mg
HbA1c (%) | N = 437 | N = 447 | N = 440
Baseline (mean) | 7.8 | 7.8 | 7.8
Change from baseline (LS mean [Intent-to-treat analysis using ANCOVA adjusted for baseline value, prior antihyperglycemic medication and baseline eGFR.]) | -0.6 | -0.5 | -0.5
Difference from glimepiride (LS mean, 95% CI) |  | 0.2 [Non-inferiority is declared when the upper bound of the two-sided 95% confidence interval (CI) for the mean difference is less than 0.3%.] (0.0, 0.3) | 0.1 (-0.0, 0.2)
Patients [N (%)] with HbA1c <7% | 208 (47.7) | 177 (39.5) | 186 (42.2)

The mean baseline body weight was 86.8 kg, 87.9 kg, and 85.6 kg in the glimepiride, STEGLATRO 5 mg, and STEGLATRO 15 mg groups, respectively. The mean changes from baseline to Week 52 were 0.6 kg, -2.6 kg, and -3.0 kg in the glimepiride, STEGLATRO 5 mg, and STEGLATRO 15 mg groups, respectively. The difference from glimepiride (95% CI) for STEGLATRO 5 mg was -3.2 kg (-3.7, -2.7) and for STEGLATRO 15 mg was -3.6 kg (-4.1, -3.1).

In Combination with Sitagliptin versus STEGLATRO Alone and Sitagliptin Alone, as Add-on to Metformin HCl

A total of 1,233 patients with type 2 diabetes mellitus with inadequate glycemic control (HbA1c between 7.5% and 11%) on metformin HCl monotherapy (≥1,500 mg/day for ≥8 weeks) participated in a randomized, double-blind, 26-week, active controlled study (NCT02099110) to evaluate the efficacy and safety of STEGLATRO 5 mg or 15 mg orally once daily in combination with sitagliptin 100 mg orally once daily compared to the individual components. Patients were randomized to one of five treatment arms: STEGLATRO 5 mg, STEGLATRO 15 mg, sitagliptin 100 mg, STEGLATRO 5 mg + sitagliptin 100 mg, or STEGLATRO 15 mg + sitagliptin 100 mg.

At Week 26, STEGLATRO 5 mg or 15 mg + sitagliptin 100 mg provided statistically significantly greater reductions in HbA1c compared to STEGLATRO (5 mg or 15 mg) alone or sitagliptin 100 mg alone. The mean change from baseline in HbA1c was -1.4% for STEGLATRO 5 mg or 15 mg + sitagliptin 100 mg versus -1.0%, for STEGLATRO 5 mg, STEGLATRO 15 mg, or sitagliptin 100 mg, respectively. More patients receiving STEGLATRO 5 mg or 15 mg + sitagliptin 100 mg achieved an HbA1c <7% (53.3% and 50.9%, for STEGLATRO 5 mg or 15 mg, respectively, + sitagliptin 100 mg) compared to the individual components (29.3%, 33.7%, and 38.5% for STEGLATRO 5 mg, STEGLATRO 15 mg, or sitagliptin 100 mg, respectively).

Add-on Combination Therapy with Metformin HCl and Sitagliptin

A total of 463 patients with type 2 diabetes mellitus inadequately controlled (HbA1c between 7% and 10.5%) on metformin HCl (≥1,500 mg/day for ≥8 weeks) and sitagliptin 100 mg once daily participated in a randomized, double-blind, multi-center, 26-week, placebo-controlled study (NCT02036515) to evaluate the efficacy and safety of STEGLATRO. Patients entered a 2-week, single-blind, placebo run-in period and were randomized to placebo, STEGLATRO 5 mg, or STEGLATRO 15 mg orally once daily.

At Week 26, treatment with STEGLATRO at 5 mg or 15 mg daily provided statistically significant reductions in HbA1c. STEGLATRO also resulted in a higher proportion of patients achieving an HbA1c <7% compared to placebo (see Table 7).

Table 7: Results at Week 26 from an Add-on Study of STEGLATRO in Combination with Metformin HCl and Sitagliptin in Patients with Type 2 Diabetes Mellitus [N includes all randomized and treated patients with a baseline measurement of the outcome variable. At Week 26, the primary HbA1c endpoint was missing for 10%, 11%, and 7% of patients and during the trial, rescue medication was initiated by 16%, 1%, and 2% of patients randomized to placebo, STEGLATRO 5 mg, and STEGLATRO 15 mg, respectively. Missing Week 26 measurements were imputed using multiple imputation with a mean equal to the baseline value of the patient. Results include measurements collected after initiation of rescue medication. For those patients who did not receive rescue medication and had values measured at 26 weeks, the mean changes from baseline for HbA1c were -0.2%, -0.8%, and -0.9% for placebo, STEGLATRO 5 mg, and STEGLATRO 15 mg, respectively.]
 | Placebo | STEGLATRO 5 mg | STEGLATRO 15 mg
HbA1c (%) | N = 152 | N = 155 | N = 152
Baseline (mean) | 8.0 | 8.1 | 8.0
Change from baseline (LS mean [Intent-to-treat analysis using ANCOVA adjusted for baseline value, prior antihyperglycemic medication and baseline eGFR.]) | -0.2 | -0.7 | -0.8
Difference from placebo (LS mean, 95% CI) |  | -0.5 [p<0.001 compared to placebo.] (-0.7, -0.3) | -0.6 (-0.8, -0.4)
Patients [N (%)] with HbA1c <7% | 31 (20.2) | 54 (34.6) | 64 (42.3)
FPG (mg/dL) | N = 152 | N = 156 | N = 152
Baseline (mean) | 169.6 | 167.7 | 171.7
Change from baseline (LS mean) | -6.5 | -25.7 | -32.1
Difference from placebo (LS mean, 95% CI) |  | -19.2 (-26.8, -11.6) | -25.6 (-33.2, -18.0)

The mean baseline body weight was 86.5 kg, 87.6 kg, and 86.6 kg in the placebo, STEGLATRO 5 mg, and STEGLATRO 15 mg groups, respectively. The mean changes from baseline to Week 26 were -1.0 kg, -3.0 kg, and -2.8 kg in the placebo, STEGLATRO 5 mg, and STEGLATRO 15 mg groups, respectively. The difference from placebo (95% CI) for STEGLATRO 5 mg was -1.9 kg (-2.6, -1.3) and for STEGLATRO 15 mg was -1.8 kg (-2.4, -1.2).

The mean baseline systolic blood pressure was 130.2 mmHg, 132.1 mmHg, and 131.6 mmHg in the placebo, STEGLATRO 5 mg, and STEGLATRO 15 mg groups, respectively. The mean changes from baseline to Week 26 were -0.2 mmHg, -3.8 mmHg, and -4.5 mmHg in the placebo, STEGLATRO 5 mg, and STEGLATRO 15 mg groups, respectively. The difference from placebo (95% CI) for STEGLATRO 5 mg was -3.7 mmHg (-6.1, -1.2) and for STEGLATRO 15 mg was -4.3 mmHg (-6.7, -1.9).

Initial Combination Therapy with Sitagliptin

A total of 291 patients with type 2 diabetes mellitus inadequately controlled (HbA1c between 8% and 10.5%) on diet and exercise participated in a randomized, double-blind, multi-center, placebo-controlled 26-week study (NCT02226003) to evaluate the efficacy and safety of STEGLATRO in combination with sitagliptin. These patients, who were not receiving any background antihyperglycemic treatment for ≥8 weeks, entered a 2-week, single-blind, placebo run-in period and were randomized to placebo, STEGLATRO 5 mg or STEGLATRO 15 mg, in combination with sitagliptin (100 mg) orally once daily.

At Week 26, treatment with STEGLATRO 5 mg and 15 mg in combination with sitagliptin at 100 mg daily provided statistically significant reductions in HbA1c compared to placebo. STEGLATRO 5 mg and 15 mg in combination with sitagliptin at 100 mg daily also resulted in a higher proportion of patients achieving an HbA1c <7% and greater reductions in FPG compared with placebo.

Add-on Combination Therapy with Insulin (with or without Metformin HCl)

In an 18-week randomized, double-blind, multi-center, placebo-controlled, glycemic sub-study of VERTIS CV (eValuation of ERTugliflozin efficacy and Safety CardioVascular, NCT01986881, study details see 14.2), a total of 1,065 patients with type 2 diabetes mellitus and established atherosclerotic cardiovascular disease with inadequate glycemic control (HbA1c between 7% and 10.5%) on background therapy of insulin ≥20 units/day (59% also on metformin HCl ≥1,500 mg/day) were randomized to placebo, STEGLATRO 5 mg or STEGLATRO 15 mg orally once daily treatment.

At Week 18, treatment with STEGLATRO at 5 mg or 15 mg daily provided statistically significant reductions in HbA1c compared to placebo (see Table 8).

Table 8: Results at Week 18 from an Add-on Study of STEGLATRO in Combination with Insulin (with or without Metformin HCl) in Patients with Type 2 Diabetes Mellitus [N includes all randomized and treated patients with a baseline measurement of the outcome variable. At Week 18, the primary HbA1c endpoint was missing for 10%, 9%, and 12% of patients and during the trial, rescue medication was initiated by 12%, 7%, and 6% of patients randomized to placebo, STEGLATRO 5 mg, and STEGLATRO 15 mg, respectively. Results include measurements collected after initiation of rescue medication. Prior to Week 18, background antidiabetic medication was held stable. Missing Week 18 measurements were imputed using multiple imputation with a mean equal to the baseline value of the patient (Return to Baseline analysis).]
 | Placebo | STEGLATRO 5 mg | STEGLATRO 15 mg
HbA1c (%) | N = 346 | N = 346 | N = 367
Baseline (mean) | 8.4 | 8.4 | 8.4
Change from baseline (LS mean [Intent-to-treat analysis using ANCOVA adjusted for baseline value, insulin stratum, and baseline eGFR.] , SE) | -0.2 (0.05) | -0.7 (0.05) | -0.7 (0.05)
Difference from placebo (LS mean, 95% CI) |  | -0.5 [p<0.001 compared to placebo.] (-0.6, -0.4) | -0.5 (-0.7, -0.4)
Patients [N (%)] with HbA1c <7% [Missing values imputed as not meeting the <7% criterion.] | 37 (10.7) | 79 (22.8) | 81 (22.1)
FPG (mg/dL) | N = 343 | N = 346 | N = 368
Baseline (mean) | 167.4 | 173.8 | 175.4
Change from baseline (LS mean, SE) | -6.3 (2.91) | -25.6 (2.90) | -29.8 (2.86)
Difference from placebo (LS mean, 95% CI) |  | -19.2 (-26.8, -11.6) | -23.4 (-30.9, -16.0)
SE: standard error.

The mean baseline body weights were 93.3 kg, 93.8 kg, and 92.1 kg in the placebo, STEGLATRO 5 mg, and STEGLATRO 15 mg groups, respectively. The mean changes from baseline to Week 18 were - 0.2 kg, -1.6 kg, and -1.9 kg in the placebo, STEGLATRO 5 mg, and STEGLATRO 15 mg groups, respectively. The differences from placebo (95% CI) for STEGLATRO 5 mg were - 1.4 kg (- 1.9, - 0.9) and for STEGLATRO 15 mg was -1.6 kg (-2.1, -1.1).

The mean baseline systolic blood pressures were 134.0 mmHg, 135.6 mmHg, and 133.7 mmHg in the placebo, STEGLATRO 5 mg, and STEGLATRO 15 mg groups, respectively. The mean changes from baseline to Week 18 were 0.7 mmHg, -2.2 mmHg, and -1.7 mmHg in the placebo, STEGLATRO 5 mg, and STEGLATRO 15 mg groups, respectively. The differences from placebo (95% CI) for STEGLATRO 5 mg was – 2.9 mmHg (-4.9, -1.0) and for STEGLATRO 15 mg were -2.5 mmHg (- 4.4, - 0.5).

Add-on Combination Therapy with Metformin HCl and Sulfonylurea

In an 18-week randomized, double-blind, multi-center, placebo-controlled, glycemic sub-study of VERTIS CV (NCT01986881, study details see 14.2), a total of 330 patients with type 2 diabetes mellitus and established atherosclerotic cardiovascular disease with inadequate glycemic control (HbA1c between 7% and 10.5%) with background therapy of metformin HCl ≥1,500 mg/day and a sulfonylurea (SU) were randomized to placebo, STEGLATRO 5 mg or STEGLATRO 15 mg orally once daily treatment.

At Week 18, treatment with STEGLATRO at 5 mg or 15 mg daily provided statistically significant reductions in HbA1c compared to placebo (see Table 9).

Table 9: Results at Week 18 from an Add-on Study of STEGLATRO in Combination with Metformin HCl and a SU in Patients with Type 2 Diabetes Mellitus [N includes all randomized and treated patients with a baseline measurement of the outcome variable. At Week 18, the primary HbA1c endpoint was missing for 9%, 8%, and 6% of patients and during the trial, rescue medication was initiated by 10%, 7%, and 3% of patients randomized to placebo, STEGLATRO 5 mg, and STEGLATRO 15 mg, respectively. Results include measurements collected after initiation of rescue medication. Missing Week 18 measurements were imputed using multiple imputation with a mean equal to the baseline value of the patient (Return to Baseline analysis).]
 | Placebo | STEGLATRO 5 mg | STEGLATRO 15 mg
HbA1c (%) | N = 116 | N = 99 | N = 113
Baseline (mean) | 8.3 | 8.4 | 8.3
Change from baseline (LS mean [Intent-to-treat analysis using ANCOVA adjusted for baseline value and baseline eGFR.] , SE) | -0.3 (0.08) | -0.8 (0.09) | -0.9 (0.08)
Difference from placebo (LS mean, 95% CI) |  | -0.6 [p<0.001 compared to placebo.] (-0.8, -0.3) | -0.7 (-0.9, -0.4)
Patients [N (%)] with HbA1c <7% [Missing values imputed as not meeting the <7% criterion.] | 17 (14.7) | 39 (39.4) | 38 (33.6)
FPG (mg/dL) | N = 117 | N = 99 | N = 113
Baseline (mean) | 177.3 | 183.5 | 174.0
Change from baseline (LS mean, SE) | -3.5 (3.65) | -31.3 (3.87) | -33.0 (3.67)
Difference from placebo (LS mean, 95% CI) |  | -27.9 (-37.8, -17.9) | -29.5 (-39.0, -19.9)
SE: standard error

The mean baseline body weights were 90.5 kg, 92.1 kg, and 92.9 kg in the placebo, STEGLATRO 5 mg, and STEGLATRO 15 mg groups, respectively. The mean changes from baseline to Week 18 were - 0.6 kg, -2.0 kg, and - 2.2 kg in the placebo, STEGLATRO 5 mg, and STEGLATRO 15 mg groups, respectively. The differences from placebo (95% CI) for STEGLATRO 5 mg were - 1.4 kg (- 2.2, - 0.7) and for STEGLATRO 15 mg was - 1.6 kg (- 2.3, - 0.9).

Use in Patients with Type 2 Diabetes Mellitus and Moderate Renal Impairment

26-Week Placebo-Controlled Study

The efficacy of STEGLATRO was assessed in a multicenter, randomized, double-blind, placebo-controlled study (NCT01986855) of patients with type 2 diabetes mellitus and moderate renal impairment (468 patients with eGFR ≥30 to <60 mL/min/1.73 m^2). In this study, 202 patients exposed to STEGLATRO (5 mg or 15 mg) had an eGFR between 45 and 60 mL/min/1.73 m^2 and 111 patients exposed to STEGLATRO (5 mg or 15 mg orally once daily) had an eGFR between 30 and 45 mL/min/1.73 m^2. The mean duration of diabetes for the study population was approximately 14 years, and the majority of patients were receiving background insulin (55.9%) and/or sulfonylurea (40.3%) therapy. Approximately 50% had a history of cardiovascular disease or heart failure.

STEGLATRO did not show efficacy in this study. The HbA1c reductions from baseline to Week 26 were not significantly different between placebo and STEGLATRO 5 mg or 15 mg [see Use in Specific Populations (8.6)].

14.2 Cardiovascular Outcomes in Patients with Type 2 Diabetes Mellitus and Established Cardiovascular Disease

The effect of STEGLATRO on cardiovascular risk in adult patients with type 2 diabetes and established atherosclerotic cardiovascular disease was evaluated in the VERTIS CV study (NCT01986881), a multicenter, multi-national, randomized, double-blind, placebo-controlled, event-driven trial. The study compared the risk of experiencing a major adverse cardiovascular event (MACE) between STEGLATRO and placebo when these were added to and used concomitantly with standard of care treatments for diabetes and atherosclerotic cardiovascular disease.

A total of 8,246 patients were randomized to placebo (N=2,747), oral once daily STEGLATRO 5 mg (N=2,752) or oral once daily STEGLATRO 15 mg (N=2,747) and followed for a median of 3 years. Approximately 88% of the study population was White, 6% Asian, and 3% Black or African American. The mean age was 64 years and approximately 70% were male.

All patients in the study had inadequately controlled type 2 diabetes mellitus at baseline (HbA1c greater than or equal to 7%). The mean duration of type 2 diabetes mellitus was 13 years, the mean HbA1c at baseline was 8.2% and the mean eGFR was 76 mL/min/1.73 m^2. At baseline, patients were treated with one (32%) or more (67%) antidiabetic medications including biguanides (metformin HCl) (76%), insulin (47%), sulfonylureas (41%) DPP-4 inhibitors (11%) and GLP-1 receptor agonists (3%).

Almost all patients (99%) had established atherosclerotic cardiovascular disease at baseline including: a documented history of coronary artery disease (76%), cerebrovascular disease (23%) or peripheral artery disease (19%). Approximately 24% patients had a history of heart failure (HF). At baseline, the mean systolic blood pressure was 133 mmHg, the mean diastolic blood pressure was 77 mmHg, the mean LDL was 89 mg/dL, and the mean HDL was 44 mg/dL. At baseline, approximately 81% of patients were treated with renin angiotensin system inhibitors, 69% with beta-blockers, 43% with diuretics, 82% with statins, 4% with ezetimibe, and 89% with antiplatelet agents.

The primary endpoint in VERTIS CV was the time to first occurrence of MACE. A major adverse cardiovascular event was defined as occurrence of either a cardiovascular death or a nonfatal myocardial infarction (MI) or a nonfatal stroke. The statistical analysis plan pre-specified that the 5 and 15 mg doses would be combined for the analysis. A Cox proportional hazards model was used to test for non-inferiority against the pre-specified risk margin of 1.3 for the hazard ratio of MACE. Type-1 error was controlled across multiple tests using a hierarchical testing strategy.

The incidence rate of MACE was similar between the STEGLATRO-treated and placebo-treated patients. The estimated hazard ratio of MACE associated with STEGLATRO relative to placebo was 0.97 with 95.6% confidence interval (0.85, 1.11). The upper bound of this confidence interval excluded a risk larger than 1.3 (Table 10). Results for the individual 5 mg and 15 mg doses were consistent with results for the combined dose group.

Table 10: Analysis of MACE and its Components from the VERTIS-CV Study [Intent-to-treat analysis set.]
Endpoint [MACE was evaluated in subjects who took at least one dose of study medication and, for subjects who discontinued study medication prior to the end of the study, censored events that occurred more than 365 days after the last dose of study medication. Other endpoints were evaluated using all randomized subjects and events that occurred any time after the first dose of study medication until the last contact date. The total number of first events was analyzed for each endpoint.] | Placebo (N=2747) |  | STEGLATRO (N=5499) |  | Hazard Ratio vs Placebo (CI) [HR and CI are based on Cox proportional hazards regression model, stratified by cohorts. For MACE a 95.6% CI is presented, for other endpoints a 95% CI is presented.]
Endpoint [MACE was evaluated in subjects who took at least one dose of study medication and, for subjects who discontinued study medication prior to the end of the study, censored events that occurred more than 365 days after the last dose of study medication. Other endpoints were evaluated using all randomized subjects and events that occurred any time after the first dose of study medication until the last contact date. The total number of first events was analyzed for each endpoint.] | N (%) | Event Rate (per 100 person-years) | N (%) | Event Rate (per 100 person-years) | Hazard Ratio vs Placebo (CI) [HR and CI are based on Cox proportional hazards regression model, stratified by cohorts. For MACE a 95.6% CI is presented, for other endpoints a 95% CI is presented.]
MACE (CV death, non-fatal MI, or non-fatal stroke) Composite | 327 (11.9) | 4.0 | 653 (11.9) | 3.9 | 0.97 (0.85, 1.11)
Components of Composite Endpoint
Non-fatal MI | 148 (5.4) | 1.6 | 310 (5.6) | 1.7 | 1.04 (0.86, 1.27)
Non-fatal Stroke | 78 (2.8) | 0.8 | 157 (2.9) | 0.8 | 1.00 (0.76, 1.32)
CV death | 184 (6.7) | 1.9 | 341 (6.2) | 1.8 | 0.92 (0.77, 1.11)
N=Number of patients, CI=Confidence interval, CV=Cardiovascular, MI=Myocardial infarction.

16 HOW SUPPLIED/STORAGE AND HANDLING

STEGLATRO (ertugliflozin) tablets are available as follows:

Strength | Description | How Supplied | NDC
5 mg tablets | pink, triangular-shaped, biconvex tablets, with “701” debossed on one side and plain on the other side | unit-of-use bottles of 30 | 0006-5363-03
5 mg tablets | pink, triangular-shaped, biconvex tablets, with “701” debossed on one side and plain on the other side | unit-of-use bottles of 90 | 0006-5363-06
15 mg tablets | red, triangular-shaped, biconvex tablets, with “702” debossed on one side and plain on the other side | unit-of-use bottles of 30 | 0006-5364-03
15 mg tablets | red, triangular-shaped, biconvex tablets, with “702” debossed on one side and plain on the other side | unit-of-use bottles of 90 | 0006-5364-06

STORAGE AND HANDLING

Store at 20°C -25°C (68°F -77°F), excursions permitted between 15°C -30°C (between 59°F -86°F) [see USP Controlled Room Temperature]. Protect from moisture. Store in a dry place.

17 PATIENT COUNSELING INFORMATION

Advise the patient to read the FDA-approved patient labeling (Medication Guide).

Diabetic Ketoacidosis in Patients with Type 1 Diabetes Mellitus and Other Ketoacidosis

Inform patients that STEGLATRO can cause potentially fatal ketoacidosis and that type 2 diabetes mellitus and pancreatic disorders (e.g., history of pancreatitis or pancreatic surgery) are risk factors.

Educate all patients on precipitating factors (such as insulin dose reduction or missed insulin doses, infection, reduced caloric intake, ketogenic diet, surgery, dehydration, and alcohol abuse) and symptoms of ketoacidosis (including nausea, vomiting, abdominal pain, tiredness, and labored breathing). Inform patients that blood glucose may be normal even in the presence of ketoacidosis.

Advise patients that they may be asked to monitor ketones. If symptoms of ketoacidosis occur, instruct patients to discontinue STEGLATRO and seek medical attention immediately [see Warnings and Precautions (5.1)].

Lower Limb Amputation

Inform patients of the potential for an increased risk of amputations. Counsel patients about the importance of routine preventative foot care. Instruct patients to monitor for new pain or tenderness, sores or ulcers, or infections involving the leg or foot and to seek medical advice immediately if such signs or symptoms develop [see Warnings and Precautions (5.2)].

Volume Depletion

Inform patients that symptomatic hypotension may occur with STEGLATRO and advise them to contact their doctor if they experience such symptoms [see Warnings and Precautions (5.3)]. Inform patients that dehydration may increase the risk for hypotension, and to have adequate fluid intake.

Serious Urinary Tract Infections

Inform patients of the potential for urinary tract infections, which may be serious. Provide them with information on the symptoms of urinary tract infections. Advise them to seek medical advice if such symptoms occur [see Warnings and Precautions (5.4)].

Hypoglycemia with Concomitant Use of Insulin or Insulin Secretagogue

Inform patients that the incidence of hypoglycemia may increase when STEGLATRO is used with insulin or an insulin secretagogue. Educate patients or caregivers on the signs and symptoms of hypoglycemia [see Warnings and Precautions (5.5)].

Necrotizing Fasciitis of the Perineum (Fournier's Gangrene)

Inform patients that necrotizing infections of the perineum (Fournier's Gangrene) have occurred with SGLT2 inhibitors. Counsel patients to promptly seek medical attention if they develop pain or tenderness, redness, or swelling of the genitals or the area from the genitals back to the rectum, along with a fever above 100.4°F or malaise [see Warnings and Precautions (5.6)].

Genital Mycotic Infections in Females (e.g., Vulvovaginitis)

Inform female patients that vaginal yeast infections may occur and provide them with information on the signs and symptoms of vaginal yeast infection. Advise them of treatment options and when to seek medical advice [see Warnings and Precautions (5.7)].

Genital Mycotic Infections in Males (e.g., Balanitis or Balanoposthitis)

Inform male patients that yeast infections of the penis (e.g., balanitis or balanoposthitis) may occur, especially in uncircumcised males. Provide them with information on the signs and symptoms of balanitis and balanoposthitis (rash or redness of the glans or foreskin of the penis). Advise them of treatment options and when to seek medical advice [see Warnings and Precautions (5.7)].

Fetal Toxicity

Advise pregnant patients of the potential risk to a fetus with treatment with STEGLATRO. Instruct patients to immediately inform their healthcare provider if pregnant or planning to become pregnant [see Use in Specific Populations (8.1)].

Lactation

Advise patients that use of STEGLATRO is not recommended while breastfeeding [see Use in Specific Populations (8.2)].

Laboratory Tests

Due to its mechanism of action, inform patients that their urine will test positive for glucose while taking STEGLATRO.

Missed Dose

Instruct patients to take STEGLATRO only as prescribed. If a dose is missed, it should be taken as soon as the patient remembers. Advise patients not to double their next dose.

Manufactured for: Merck Sharp & Dohme LLC
Rahway, NJ 07065, USA

For patent information: www.msd.com/research/patent

Copyright © 2017-2024 Merck & Co., Inc., Rahway, NJ, USA, and its affiliates.
All rights reserved.

uspi-mk8835-t-2412r010

Medication Guide
STEGLATRO® [steh-GLA-troh]
(ertugliflozin)
tablets, for oral use

Read this Medication Guide carefully before you start taking STEGLATRO and each time you get a refill. There may be new information. This information does not take the place of talking with your healthcare provider about your medical condition or your treatment.

What is the most important information I should know about STEGLATRO? STEGLATRO may cause serious side effects, including:

- Diabetic ketoacidosis (increased ketones in your blood or urine) in people with type 1 diabetes and other ketoacidosis. STEGLATRO can cause ketoacidosis that can be life-threatening and may lead to death. Ketoacidosis is a serious condition which needs to be treated in a hospital. People with type 1 diabetes have a high risk of getting ketoacidosis. People with type 2 diabetes or pancreas problems also have an increased risk of getting ketoacidosis. Ketoacidosis can also happen in people who: are sick, cannot eat or drink as usual, skip meals, are on a diet high in fat and low in carbohydrates (ketogenic diet), take less than the usual amount of insulin or miss insulin doses, drink too much alcohol, have a loss of too much fluid from the body (volume depletion), or who have surgery. Ketoacidosis can happen even if your blood sugar is less than 250 mg/dL. Your healthcare provider may ask you to periodically check ketones in your urine or blood.
  Stop taking STEGLATRO and call your healthcare provider or get medical help right away if you get any of the following. If possible, check for ketones in your urine or blood, even if your blood sugar is less than 250 mg/dL:

- nausea
- vomiting
- stomach-area (abdominal) pain

- tiredness
- trouble breathing
- ketones in your urine or blood

- Amputations. STEGLATRO may increase your risk of lower limb amputations.
  You may be at a higher risk of lower limb amputation if you:
  - have a history of amputation
  - have had blocked or narrowed blood vessels, usually in your leg
  - have damage to the nerves (neuropathy) in your leg
  - have had diabetic foot ulcers or sores

Call your healthcare provider right away if you have new pain or tenderness, any sores, ulcers, or infections in your leg or foot. Your healthcare provider may decide to stop your STEGLATRO for a while if you have any of these signs or symptoms. Talk to your healthcare provider about proper foot care.

- Dehydration. STEGLATRO can cause some people to become dehydrated (the loss of body water and salt). Dehydration may cause you to feel dizzy, faint, lightheaded, or weak, especially when you stand up (orthostatic hypotension). There have been reports of sudden worsening of kidney function in people who are taking STEGLATRO.

You may be at risk of dehydration if you:

- take medicines to lower your blood pressure, including water pills (diuretics)
- are on a low sodium (salt) diet
- have kidney problems
- are 65 years of age or older

Talk to your healthcare provider about what you can do to prevent dehydration including how much fluid you should drink on a daily basis. Call your healthcare provider right away if you reduce the amount of food or liquid you drink, for example if you are sick or cannot eat, or you start to lose liquids from your body, for example from vomiting, diarrhea or being in the sun too long.

- Vaginal yeast infection. Symptoms of a vaginal yeast infection include:
  - vaginal odor
  - white or yellowish vaginal discharge (discharge may be lumpy or look like cottage cheese)
  - vaginal itching
- Yeast infection of the penis (balanitis or balanoposthitis). Swelling of an uncircumcised penis may develop that makes it difficult to pull back the skin around the tip of the penis. Other symptoms of yeast infection of the penis include:

- redness, itching, or swelling of the penis
- foul smelling discharge from the penis

- rash of the penis
- pain in the skin around your penis

Talk to your healthcare provider about what to do if you get symptoms of a yeast infection of the vagina or penis. Your healthcare provider may suggest you use an over-the-counter antifungal medicine. Talk to your healthcare provider right away if you use an over-the-counter antifungal medicine and your symptoms do not go away.

What is STEGLATRO?

- STEGLATRO is a prescription medicine used in adults with type 2 diabetes to improve blood sugar (glucose) control along with diet and exercise.
- STEGLATRO is not recommended to decrease blood sugar (glucose) in people with type 1 diabetes.
- It is not known if STEGLATRO is safe and effective in children under 18 years of age.

Who should not take STEGLATRO?
Do not take STEGLATRO if you:

- are allergic to ertugliflozin or any of the ingredients in STEGLATRO. See the end of this Medication Guide for a list of ingredients in STEGLATRO. Symptoms of a serious allergic reaction to STEGLATRO may include:
  - skin rash
  - raised red patches on your skin (hives)
  - swelling of the face, lips, tongue, and throat that may cause difficulty in breathing or swallowing

If you have any of these symptoms, stop taking STEGLATRO and call your healthcare provider right away or go to the nearest hospital emergency room.

Before you take STEGLATRO, tell your healthcare provider about all of your medical conditions, including if you:

- have type 1 diabetes or have had diabetic ketoacidosis.
- have a decrease in your insulin dose.
- have a serious infection.
- have a history of infection of the vagina or penis.
- have a history of amputation.
- have had blocked or narrowed blood vessels, usually in your leg.
- have damage to the nerves (neuropathy) in your leg.
- have had diabetic foot ulcers or sores.
- have kidney problems.
- have liver problems.
- have a history of urinary tract infections or problems with urination.
- are on a low sodium (salt) diet. Your healthcare provider may change your diet or your dose.
- are going to have surgery. Your healthcare provider may stop your STEGLATRO before you have surgery. Talk to your healthcare provider if you are having surgery about when to stop taking STEGLATRO and when to start it again.
- are eating less or there is a change in your diet.
- are dehydrated.
- have or have had problems with your pancreas, including pancreatitis or surgery on your pancreas.
- drink alcohol very often or drink a lot of alcohol in the short term (“binge” drinking).
- have ever had an allergic reaction to STEGLATRO.
- are pregnant or plan to become pregnant. STEGLATRO may harm your unborn baby. If you become pregnant while taking STEGLATRO, your healthcare provider may switch you to a different medicine to control your blood sugar. Talk to your healthcare provider about the best way to control your blood sugar if you plan to become pregnant or while you are pregnant.
- are breastfeeding or plan to breastfeed. It is not known if STEGLATRO passes into your breast milk. You should not breastfeed if you take STEGLATRO.

Tell your healthcare provider about all of the medicines you take, including prescription and over-the-counter medicines, vitamins, and herbal supplements.
STEGLATRO may affect the way other medicines work, and other medicines may affect how STEGLATRO works.
Know the medicines you take. Keep a list of them to show your healthcare provider and pharmacist when you get a new medicine.

How should I take STEGLATRO?

- Take STEGLATRO by mouth 1 time in the morning each day, with or without food, exactly as your healthcare provider tells you to take it.
- Your healthcare provider may tell you to take STEGLATRO along with other diabetes medicines. Low blood sugar can happen more often when STEGLATRO is taken with certain other diabetes medicines. See “What are the possible side effects of STEGLATRO?”.
- If you miss a dose, take it as soon as you remember. If it is almost time for your next dose, skip the missed dose and take the medicine at the next regularly scheduled time. Do not take 2 doses of STEGLATRO at the same time. Talk with your healthcare provider if you have questions about a missed dose.
- If you take too much STEGLATRO, call your healthcare provider or go to the nearest hospital emergency room right away.
- When your body is under some types of stress, such as fever, trauma (such as a car accident), infection, or surgery, the amount of diabetes medicine you need may change. Tell your healthcare provider right away if you have any of these conditions and follow your healthcare provider’s instructions.
- STEGLATRO will cause your urine to test positive for glucose.
- Your healthcare provider may do certain blood tests before you start STEGLATRO and during treatment as needed. Your healthcare provider may change your dose of STEGLATRO based on the results of your blood tests.

What are the possible side effects of STEGLATRO?
STEGLATRO may cause serious side effects, including:
See "What is the most important information I should know about STEGLATRO?"

- Serious urinary tract infections. Serious urinary tract infections that may lead to hospitalization have happened in people who are taking STEGLATRO. Tell your healthcare provider if you have any signs or symptoms of a urinary tract infection such as a burning feeling when passing urine, a need to urinate often, the need to urinate right away, pain in the lower part of your stomach (pelvis), or blood in the urine. Sometimes people may also have a fever, back pain, nausea, or vomiting.
- Low blood sugar (hypoglycemia). If you take STEGLATRO with another medicine that can cause low blood sugar such as a sulfonylurea or insulin, your risk of getting low blood sugar is higher. The dose of your sulfonylurea or insulin may need to be lowered while you take STEGLATRO. Signs and symptoms of low blood sugar may include:

- headache
- confusion
- hunger
- shaking or feeling jittery

- drowsiness
- dizziness
- fast heartbeat

- weakness
- sweating
- irritability

- A rare but serious bacterial infection that causes damage to the tissue under the skin (necrotizing fasciitis) in the area between and around the anus and genitals (perineum). Necrotizing fasciitis of the perineum has happened in women and men who take medicines that lower blood sugar in the same way as STEGLATRO. Necrotizing fasciitis of the perineum may lead to hospitalization, may require multiple surgeries, and may lead to death. Seek medical attention immediately if you have fever above 100.4°F or you are feeling very weak, tired or uncomfortable (malaise) and you develop any of the following symptoms in the area between and around your anus and genitals:

- pain or tenderness

- swelling

- redness of skin (erythema)

- Serious allergic reaction. If you have any symptoms of a serious allergic reaction, stop taking STEGLATRO and call your healthcare provider right away or go to the nearest hospital emergency room. See “Who should not take STEGLATRO?”. Your healthcare provider may give you a medicine for your allergic reaction and prescribe a different medicine for your diabetes.

The most common side effects of STEGLATRO include:

- vaginal yeast infections and yeast infections of the penis (See "What is the most important information I should know about STEGLATRO?")
- changes in urination, including urgent need to urinate more often, in larger amounts, or at night

These are not all the possible side effects of STEGLATRO.
Call your healthcare provider for medical advice about side effects. You may report side effects to FDA at 1-800-FDA-1088.

How should I store STEGLATRO?

- Store STEGLATRO at room temperature between 68°F to 77°F (20°C to 25°C).
- Keep STEGLATRO dry.

Keep STEGLATRO and all medicines out of the reach of children.

General information about the safe and effective use of STEGLATRO.
Medicines are sometimes prescribed for purposes other than those listed in a Medication Guide. Do not use STEGLATRO for a condition for which it was not prescribed. Do not give STEGLATRO to other people, even if they have the same symptoms that you have. It may harm them. You can ask your pharmacist or healthcare provider for information about STEGLATRO that is written for health professionals.
For more information about STEGLATRO, go to www.steglatro.com or call 1-800-622-4477.

What are the ingredients in STEGLATRO?
Active ingredient: ertugliflozin.
Inactive ingredients: microcrystalline cellulose, lactose monohydrate, sodium starch glycolate, and magnesium stearate. The tablet film coating contains the following inactive ingredients: hypromellose, lactose monohydrate, macrogol, triacetin, titanium dioxide, and iron oxide red.

Manufactured for: Merck Sharp & Dohme LLC
Rahway, NJ 07065, USA
For patent information, go to: www.msd.com/research/patent
Copyright © 2017-2023 Merck & Co., Inc., Rahway, NJ, USA, and its affiliates.
All rights reserved.
usmg-mk8835-t-2309r006

This Medication Guide has been approved by the U.S. Food and Drug Administration.

Revised: 09/2023

PRINCIPAL DISPLAY PANEL - 5 mg Tablet Bottle Label

NDC 0006-5363-03

Steglatro®
(ertugliflozin) tablets

5 mg

Dispense the accompanying Medication Guide
to each patient.

Each tablet contains 6.48 mg ertugliflozin L-pyroglutamic
acid (equivalent to 5 mg ertugliflozin).

Rx only

30 Tablets

PRINCIPAL DISPLAY PANEL - 15 mg Tablet Bottle Label

NDC 0006-5364-03

Steglatro®
(ertugliflozin) tablets

15 mg

Dispense the accompanying Medication Guide
to each patient.

Each tablet contains 19.43 mg ertugliflozin L-pyroglutamic
acid (equivalent to 15 mg ertugliflozin).

Rx only

30 Tablets